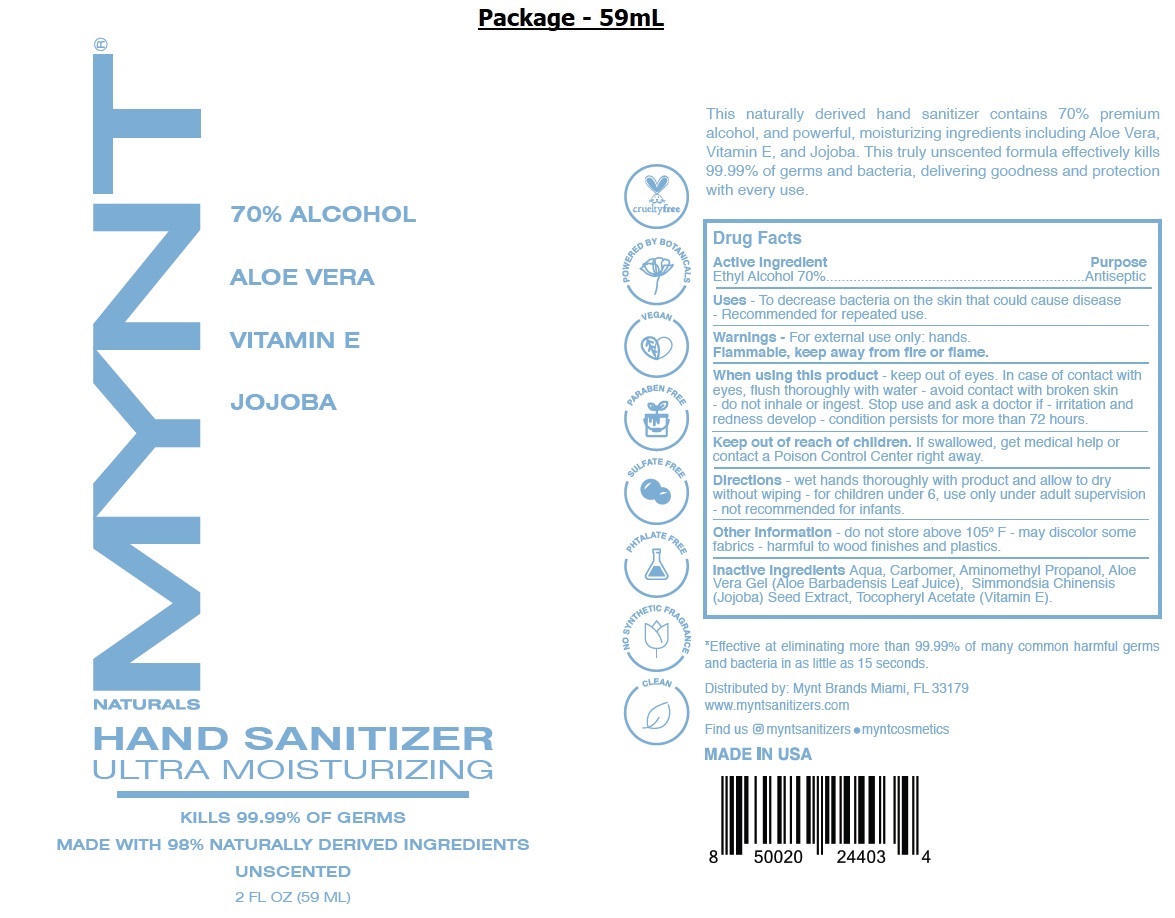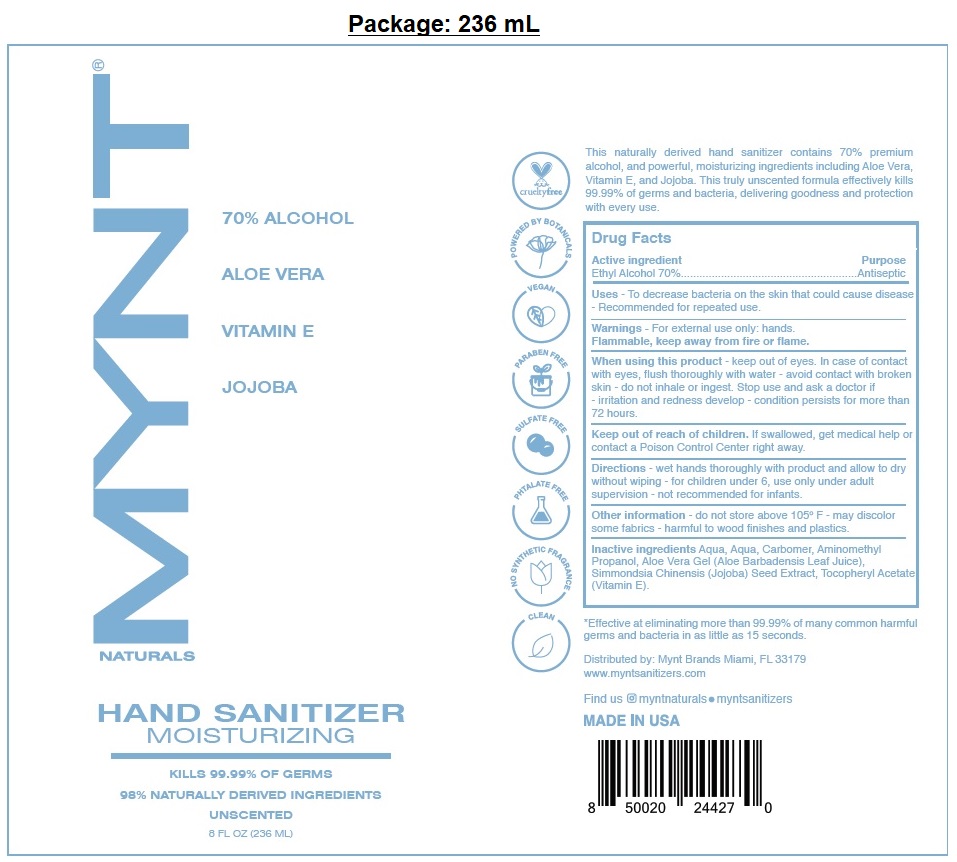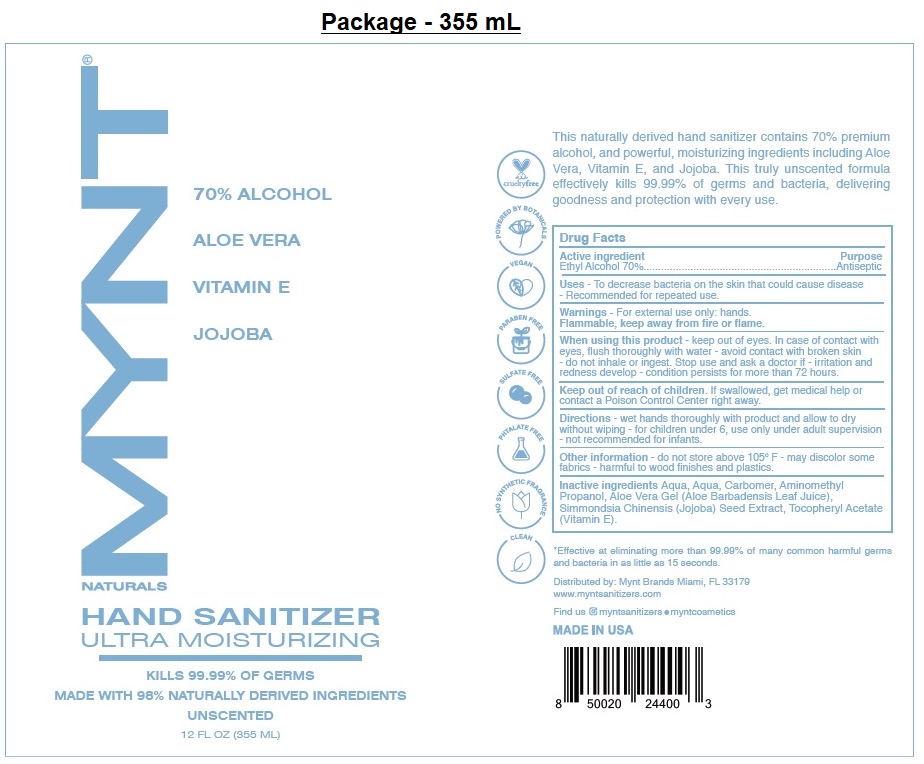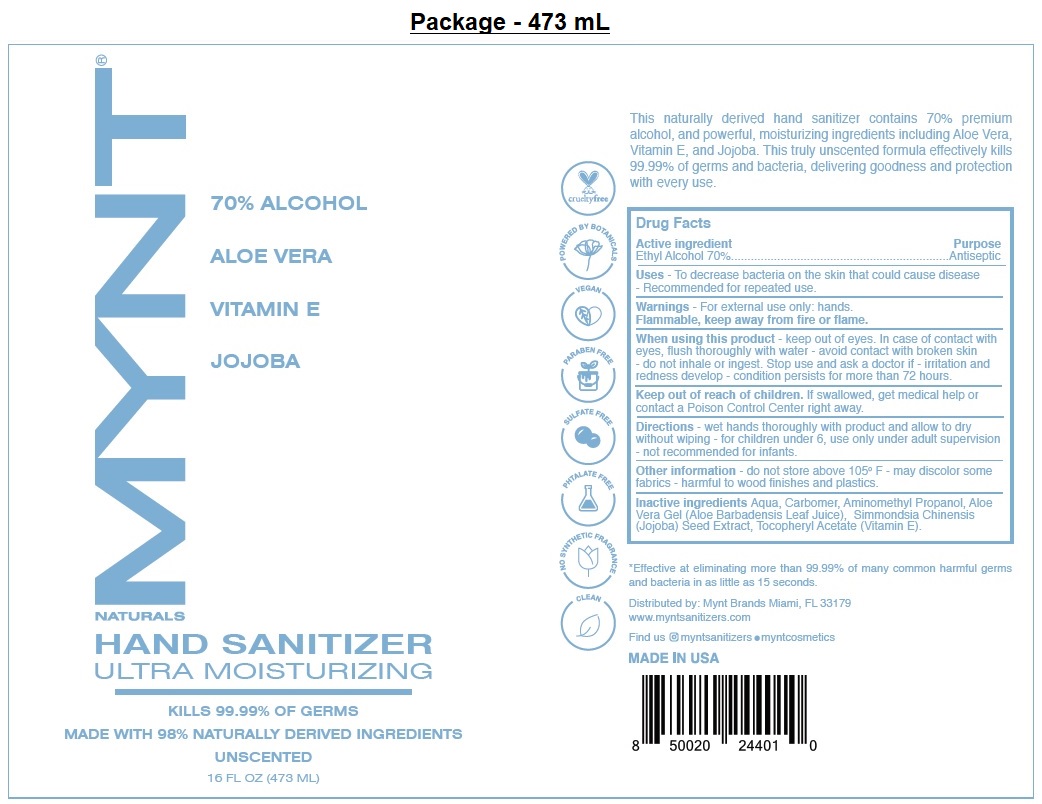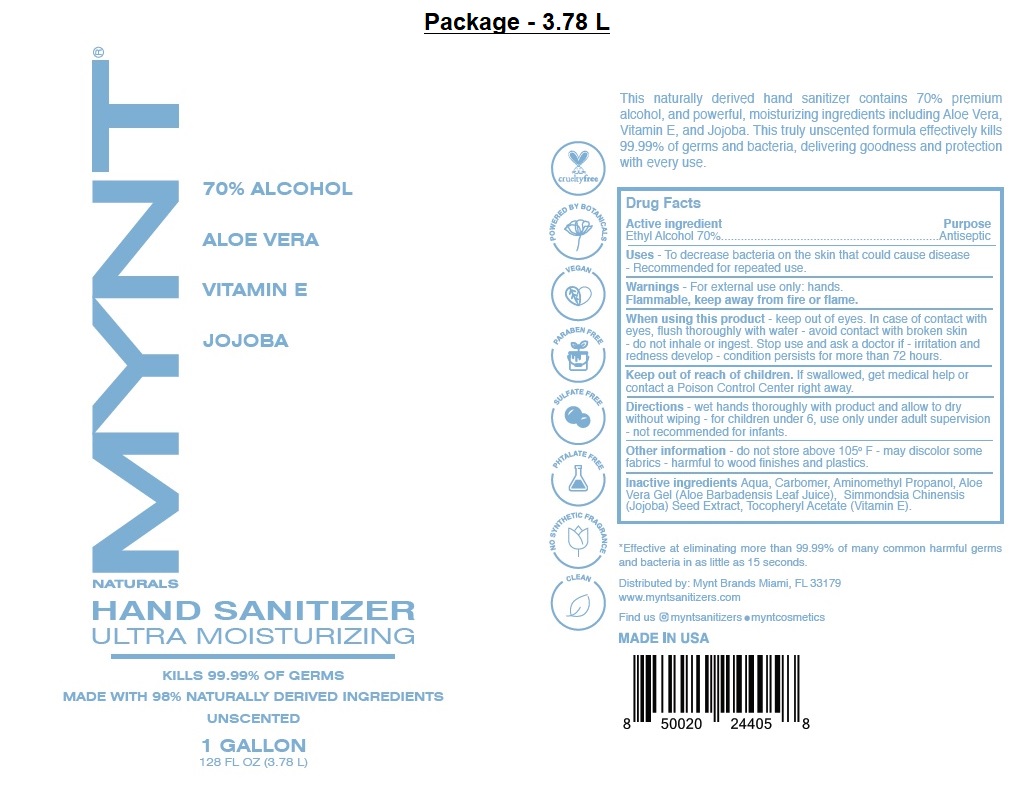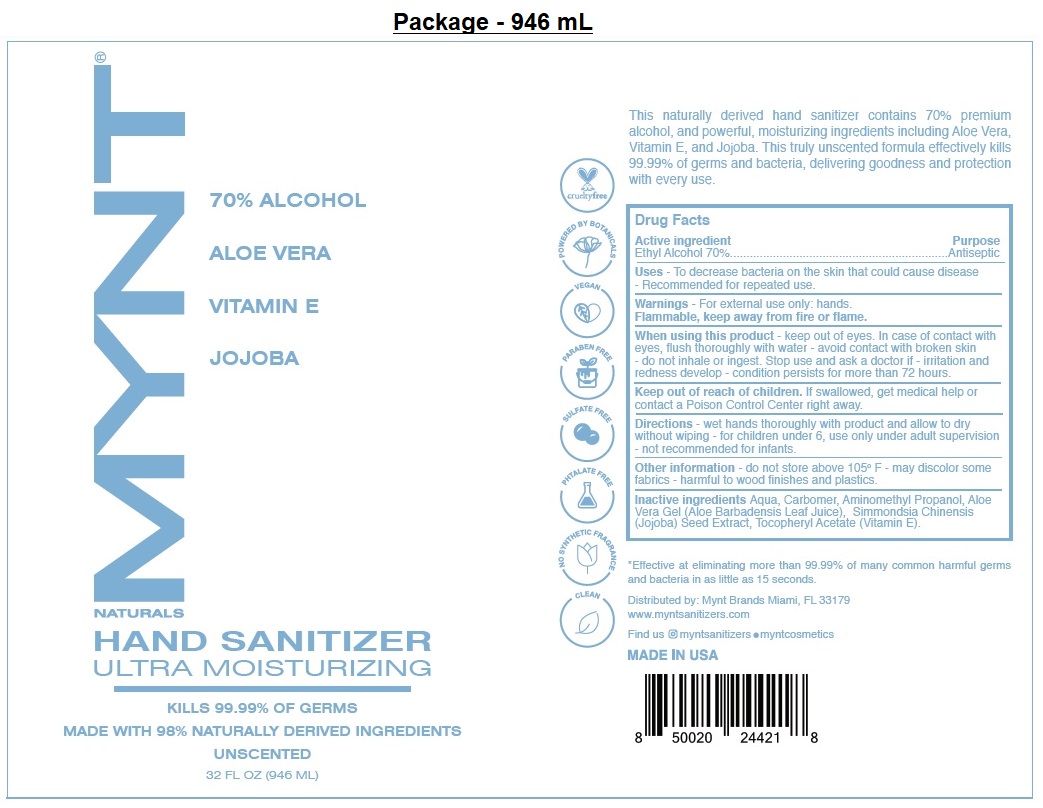 DRUG LABEL: MYNT NATURALS Hand Sanitizer Moisturizing
NDC: 79442-105 | Form: GEL
Manufacturer: Prive International Inc.
Category: otc | Type: HUMAN OTC DRUG LABEL
Date: 20200930

ACTIVE INGREDIENTS: ALCOHOL 70 mL/100 mL
INACTIVE INGREDIENTS: WATER; CARBOMER HOMOPOLYMER, UNSPECIFIED TYPE; AMINOMETHYLPROPANOL; ALOE VERA LEAF; SIMMONDSIA CHINENSIS SEED; .ALPHA.-TOCOPHEROL ACETATE

MYNT® NATURALS HAND SANITIZER MOISTURIZING UNSCENTED

Active ingredient

Ethyl Alcohol 70%

Purpose

Antiseptic

INDICATIONS AND USAGE

Uses - To decrease bacteria on the skin that could cause disease - Recommended for repeated use.

Warnings - For external use only: hands.

Flammable, keep away from fire or flame.

When using this product - keep out of eyes. In case of contact with eyes, flush thoroughly with water - avoid contact with broken skin - do not inhale or ingest. Stop use and ask a doctor if - irritation and redness develop - condition persists for more than 72 hours.

Keep out of reach of children. If swallowed, get medical help or contact a Poison Control Center right away.

DOSAGE AND ADMINISTRATION

Directions - wet hands thoroughly with product and allow to dry without wiping - for children under 6, use only under adult supervision - not recommended for infants.

Other information - do not store above 105° F - may discolor some fabrics - harmful to wood finishes and plastics.

INACTIVE INGREDIENT

Inactive ingredients Aqua, Carbomer, Aminomethyl Propanol, Aloe Vera Gel (Aloe Barbadensis Leaf Juice), Simmondsia Chinensis (Jojoba) Seed Extract, Tocopheryl Acetate (Vitamin E).

70% ALCOHOL

ALOE VERA

VITAMIN E

JOJOBA

KILLS 99.99% OF GERMS

MADE WITH 98% NATURALLY DERIVED INGREDIENTS

UNSCENTED

cruelty free

POWERED BY BOTANICALS

VEGAN

PARABEN FREE

SULFATE FREE

PHTALATE FREE

NO SYNTHETIC FRAGRANCE

CLEAN

This naturally derived hand sanitizer contains 70% premium alcohol, and powerful, moisturizing ingredients including Aloe Vera, Vitamin E, and Jojoba. This truly unscented formula effectively kills 99.99% of germs and bacteria, delivering goodness and protection with every use.

*Effective at eliminating more than 99.99% of many common harmful germs and bacteria in as little as 15 seconds.

Distributed by: Mynt Brands Miami, FL 33179

www.myntsanitizers.com

Find us myntsanitizers • myntcosmetics

MADE IN USA